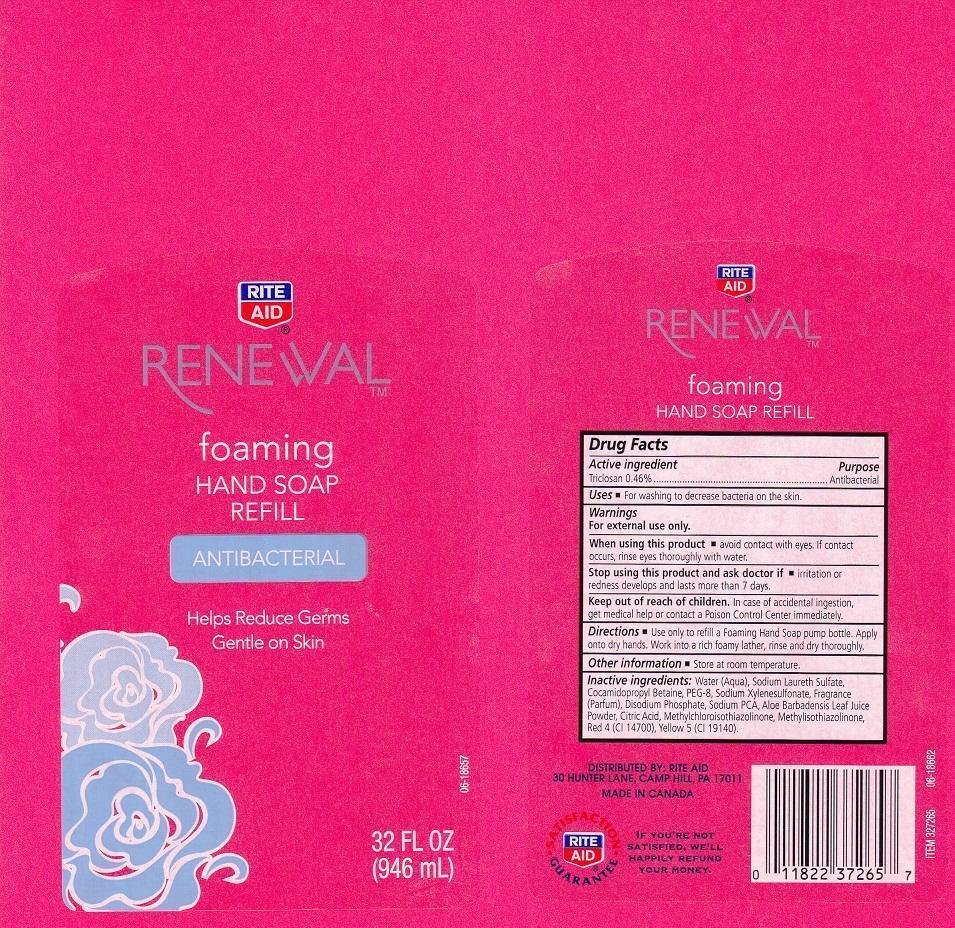 DRUG LABEL: RITE AID RENEWAL
NDC: 11822-1793 | Form: LIQUID
Manufacturer: RITE AID CORPORATION
Category: otc | Type: HUMAN OTC DRUG LABEL
Date: 20130419

ACTIVE INGREDIENTS: TRICLOSAN 4.6 mg/1 mL
INACTIVE INGREDIENTS: WATER; SODIUM LAURETH SULFATE; COCAMIDOPROPYL BETAINE; POLYETHYLENE GLYCOL 400; SODIUM XYLENESULFONATE; SODIUM PHOSPHATE, DIBASIC, ANHYDROUS; SODIUM PYRROLIDONE CARBOXYLATE; ALOE VERA LEAF; CITRIC ACID MONOHYDRATE; METHYLCHLOROISOTHIAZOLINONE; METHYLISOTHIAZOLINONE; FD&C RED NO. 4; FD&C YELLOW NO. 5

DRUG FACTS

ACTIVE INGREDIENT

TRICLOSAN 0.46%

PURPOSE

ANTIBACTERIAL

USES

FOR WASHING TO DECREASE BACTERIA ON THE SKIN.

WARNINGS

FOR EXTERNAL USE ONLY.

WHEN USING THIS PRODUCT

AVOID CONTACT WITH EYES. IF CONTACT OCCURS, RINSE EYES THOROUGHLY WITH WATER.

STOP USING THIS PRODUCT AND ASK DOCTOR IF

IRRITATION OR REDNESS DEVELOPS AND LASTS MORE THAN 7 DAYS.

KEEP OUT OF REACH OF CHILDREN

IN CASE OF ACCIDENTAL INGESTION, GET MEDICAL HELP OR CONTACT A POISON CONTROL CENTER IMMEDIATELY.

DIRECTIONS

USE ONLY TO REFILL A FOAMING HAND SOAP PUMP BOTTLE. APPLY ONTO DRY HANDS. WORK INTO A RICH FOAMY LATHER, RINSE AND DRY THOROUGHLY.

OTHER INFORMATION

STORE AT ROOM TEMPERATURE.

INACTIVE INGREDIENTS:

WATER (AQUA), SODIUM LAURETH SULFATE, COCAMIDOPROPYL BETAINE, PEG-8, SODIUM XYLENESULFONATE, FRAGRANCE (PARFUM), DISODIUM PHOSPHATE, SODIUM PCA, ALOE BARBADENSIS LEAF JUICE POWDER, CITRIC ACID, METHYLCHLOROISOTHIAZOLINONE, METHYLISOTHIAZOLINONE, RED 4 (CI 14700), YELLOW 5 (CI 19140).